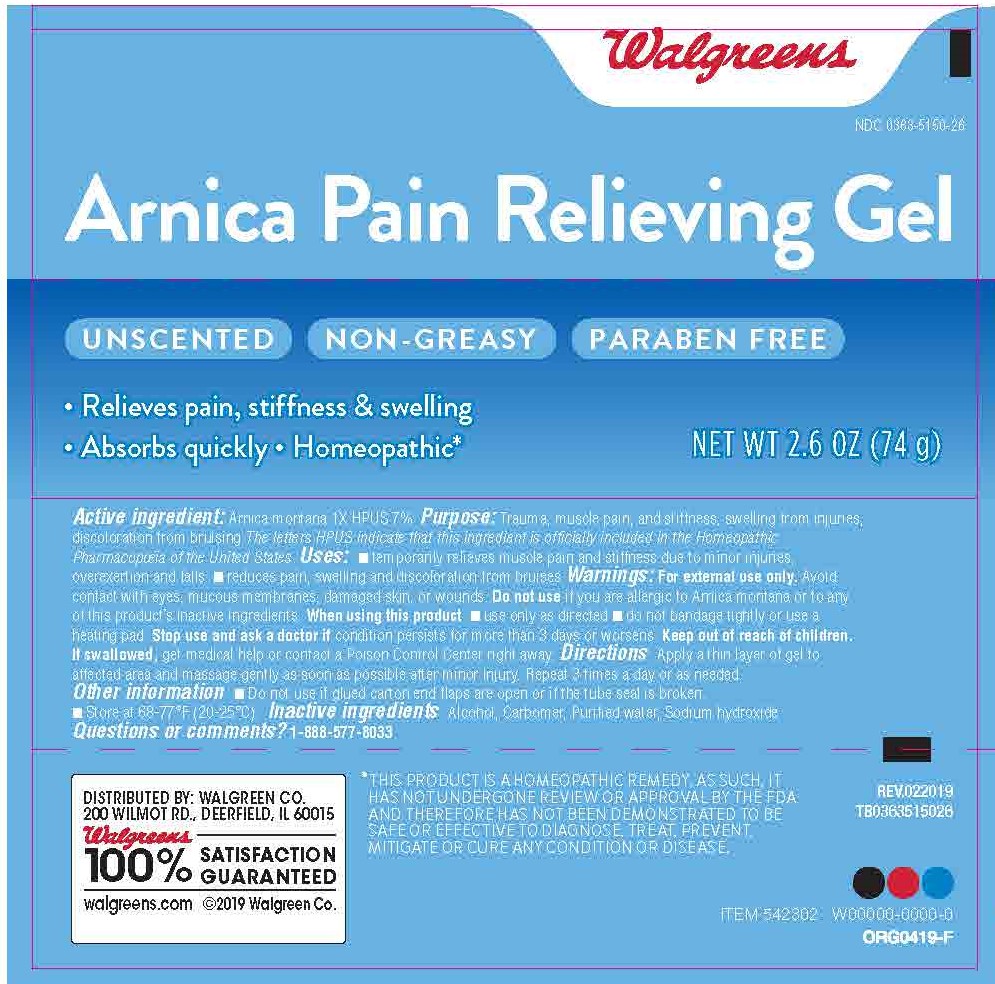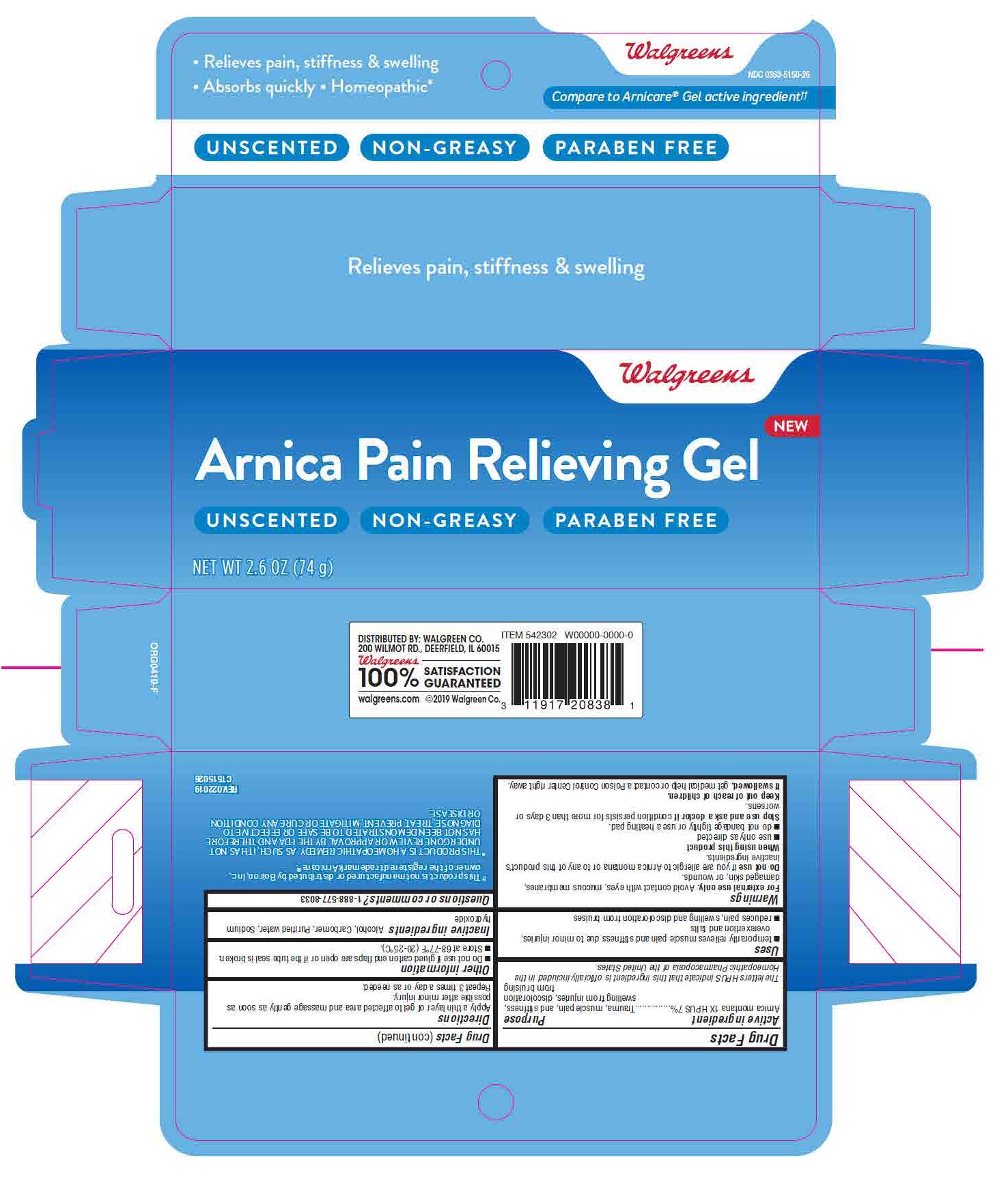 DRUG LABEL: Arnica Montana
NDC: 0363-5150 | Form: GEL
Manufacturer: WALGREENS CO.
Category: homeopathic | Type: HUMAN OTC DRUG LABEL
Date: 20220412

ACTIVE INGREDIENTS: ARNICA MONTANA 1 [hp_X]/1 g
INACTIVE INGREDIENTS: ALCOHOL; WATER; SODIUM HYDROXIDE; CARBOMER 940

Walgreens Arnica Pain Relieving Gel
Arnica Montana1X HPUS 7%

ACTIVE INGREDIENT

Arnica montana 1X HPUS 7%

INACTIVE INGREDIENT

alcohol, carbomer, purified water, sodium hydroxide

DOSAGE AND ADMINISTRATION

Apply a thin layer of gel to affected area and massage gently as soon as possible after minor injury. Repeat 3 times a day or as needed.

INDICATIONS AND USAGE

temporarily relieves muscle pain and stiffness due to minor injuries, overexertion and falls, reduces pain, swelling and discoloration from bruises

WARNINGS

For external use only

When using this product avoid contact with eyes, mucous membranes, damaged skin, or wounds.

Do not use if you are allergic to Arnica montana or to any of this product’s inactive ingredients.

When using this product use only as directed, do not bandage tightly or use a heating pad.

Stop use and ask a doctor if condition persists for more than 3 days or worsens.

Keep out of reach of children.

If swallowed, get medical help or contact a Poison Control Center right away.

Keep out of reach of children.

If swallowed, get medical help or contact a Poison Control Center right away.

PURPOSE

Trauma, muscle pain, and stiffness, swelling from injuries, discoloration from bruising

Do not use if glued carton end flaps are open or if the tube seal is broken.

Store at 68-77 F (20-25 C).